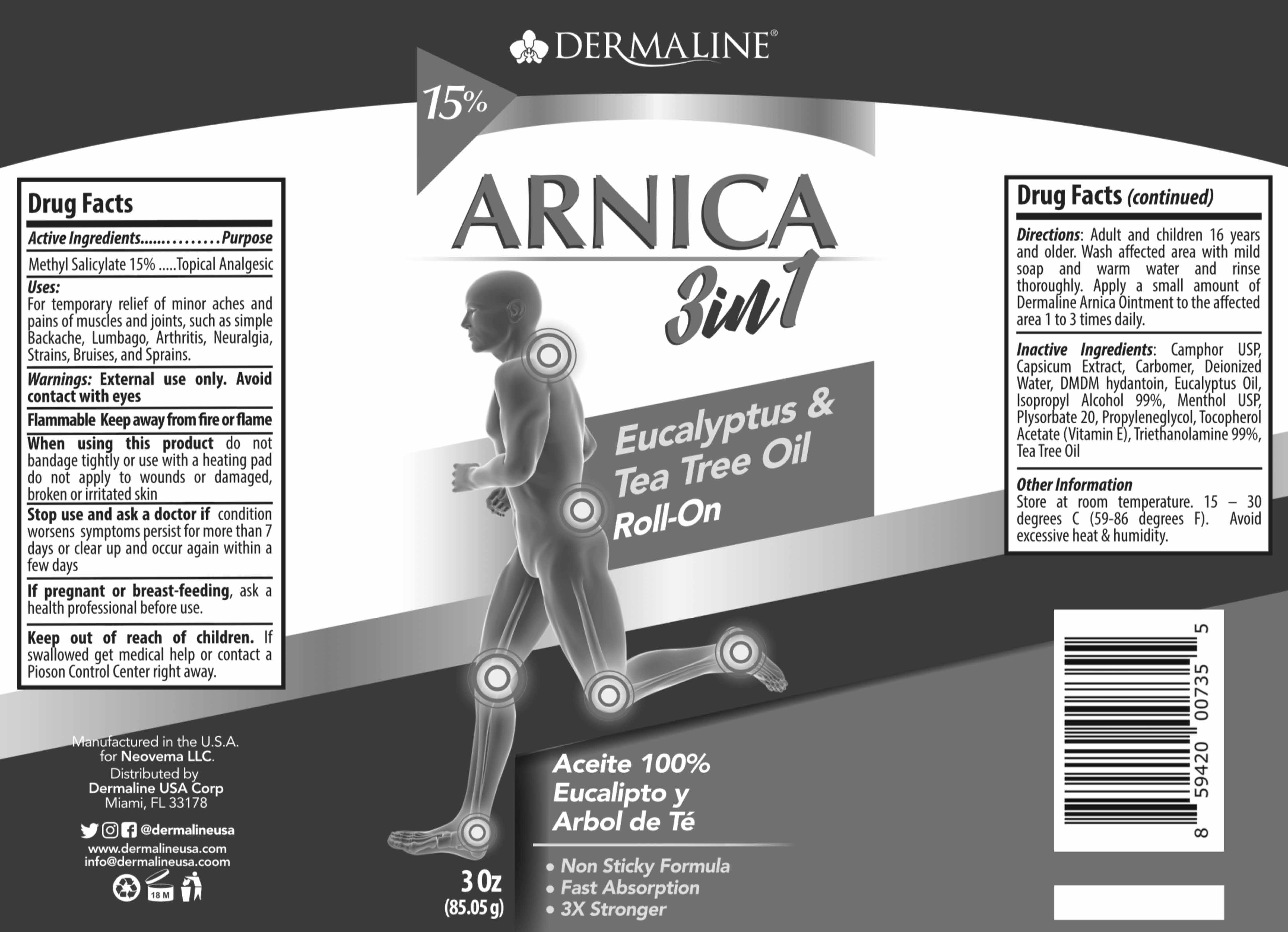 DRUG LABEL: Topical Analgesic
NDC: 82165-107 | Form: EMULSION
Manufacturer: Dermaline USA Corp
Category: otc | Type: HUMAN OTC DRUG LABEL
Date: 20220426

ACTIVE INGREDIENTS: METHYL SALICYLATE 15 g/100 g
INACTIVE INGREDIENTS: .ALPHA.-TOCOPHEROL ACETATE, D-; POLYSORBATE 20; TRIETHANOLAMINE MYRISTATE; TEA TREE OIL; CAMPHOR (SYNTHETIC); WATER; DMDM HYDANTOIN; EUCALYPTUS OIL; CARBOMER 940; MENTHOL; PROPYLENE GLYCOL; CAPSICUM OLEORESIN; ISOPROPYL ALCOHOL

Dermaline 3 in1 Roll On

ACTIVE INGREDIENT

Methyl Salicylate 15%

PURPOSE

Topical Analgesic

INSTRUCTIONS FOR USE

Uses: For temporary relief of minor aches and pains of muscles and joints, such as simple backahe, lumbago, arthritis, neuralgia, strains, bruises, and sprains

WARNINGS

Warning: External use only. Keep out of reach of children. Avoid direct contact with eyes. In case of eye contact, flush thoroughly with water. Discontinue use if irritation occurs.

Do not use on wounds or damaged skin, with a bandage, with heating pad, over extensive areas of the body, on children under 16 years of age unless directed by a doctor. If pregnant or breast-feeding ask a health professional before use. In case of accidental ingestion, get medical help or contact a Poison Control center immediately.

INDICATIONS AND USAGE

Directions: Adult and children 16 years and older. Wash affected area with mild soap and warm water and rinse throughly. Apply a small amount of Dermaline Arnica Ointment to the affected area 1 to 3 times daily.

INACTIVE INGREDIENT

Camphor, Capsicum Extract, Carbomer, Deionized Water, DMDM hydantoin, Eucalyptus Oil, Isopropyl Alcohol, Menthol, Polysorbate 20, Propyleneglycol, Tocopherol Acetate, Triethanolamine, Tea Tree Oil

OTHER SAFETY INFORMATION

Store at room temperature. 15 - 30 degrees C (59-86 degrees F). Avoid excessive heat & humidity

Keep out of reach of children

DOSAGE AND ADMINISTRATION

Directions: Adult and children 16 years and older. Wash affected area with mild soap and warm water and rinse throughly. Apply a small amount of Dermaline Arnica Ointment to the affected area 1 to 3 times daily.